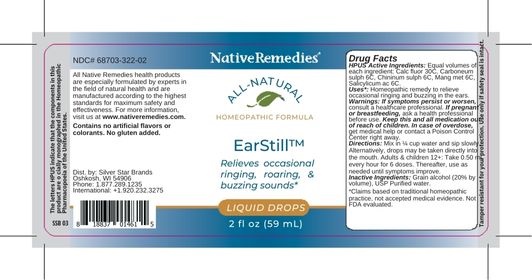 DRUG LABEL: EarStill
NDC: 68703-322 | Form: LIQUID
Manufacturer: Silver Star Brands
Category: homeopathic | Type: HUMAN OTC DRUG LABEL
Date: 20250101

ACTIVE INGREDIENTS: SALICYLIC ACID 6 [hp_C]/59 mL; CARBON DISULFIDE 6 [hp_C]/59 mL; QUININE SULFATE 6 [hp_C]/59 mL; MANGANESE 6 [hp_C]/59 mL; CALCIUM FLUORIDE 30 [hp_C]/59 mL
INACTIVE INGREDIENTS: ALCOHOL; WATER

NativeRemedies® EarStill™

HPUS Active Ingredients: Equal volumnes of each ingredient: Calc fluor 30C, Carboneum sulph 6C, Chininum sulph 6C, Mang met 6C, Salicylicum ac 6C.

Uses*:

Uses*: Homeopathic remedy to relieve occasional ringing and buzzing in the ears.

*Claims based on traditional homeopathic practice, not accepted medical evidence. Not FDA evaluated.

Warnings

Warnings: If symptoms persist or worsen, consult a healthcare professional. If pregnant or breastfeeding, ask a healthcare professional before use. Keep this and all medication out of reach of children. In case of overdose, get medical help or contact a Poison Control Center right away.

Directions

Directions: Mix in 1/4 cup water and sip slowly. Alternatively, drops may be taken directly into the mouth. Adults & children 12+: Take 0.50 mL every hour for 6 doses. Thereafter, use as needed until symptoms improve.

OTHER SAFETY INFORMATION

Contains no artificial flavors or colorants. No gluten added.

Tamper resistant for your protection. Use only if safety seals is intact.

Inactive Ingredients

Inactive Ingredients: Grain alcohol (20% by volume), USP Purified water

KEEP OUT OF REACH OF CHILDREN

Keep this and all medication out of reach of children.

PREGNANCY OR BREAST FEEDING

If pregnant or breastfeeding, ask a healthcare professional before use.

PURPOSE

Relieves occasional ringin, roaring, & buzzing sounds*